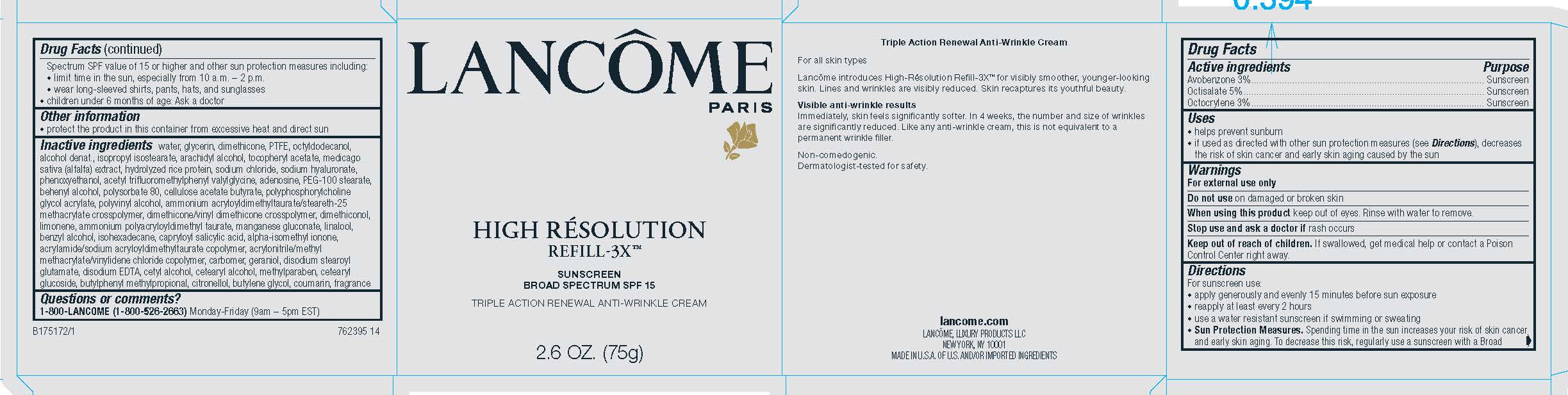 DRUG LABEL: Lancome Paris High Resolution Refill 3X Triple Action Renewal Anti Wrinkle Broad Spectrum SPF 15 Sunscreen
NDC: 49967-502 | Form: CREAM
Manufacturer: L'Oreal USA Products Inc
Category: otc | Type: HUMAN OTC DRUG LABEL
Date: 20231230

ACTIVE INGREDIENTS: Avobenzone 30 mg/1 g; Octisalate 50 mg/1 g; Octocrylene 30 mg/1 g
INACTIVE INGREDIENTS: WATER; GLYCERIN; DIMETHICONE; POLYTETRAFLUOROETHYLENE; OCTYLDODECANOL; ALCOHOL; ISOPROPYL ISOSTEARATE; ARACHIDYL ALCOHOL; .ALPHA.-TOCOPHEROL ACETATE, D-; SODIUM CHLORIDE; HYALURONATE SODIUM; PHENOXYETHANOL; ACETYL TRIFLUOROMETHYLPHENYL VALYLGLYCINE, DL-; ADENOSINE; PEG-100 STEARATE; DOCOSANOL; POLYSORBATE 80; CELLABURATE (MW 12000, 32% BUTYRYL, 18% ACETYL); POLYVINYL ALCOHOL (100000 MW); DIMETHICONE/VINYL DIMETHICONE CROSSPOLYMER (HARD PARTICLE); DIMETHICONOL (100000 CST); LIMONENE, (+)-; MANGANESE; GLUCONATE ION; LINALOOL, (+/-)-; BENZYL ALCOHOL; ISOHEXADECANE; CAPRYLOYL SALICYLIC ACID; ISOMETHYL-.ALPHA.-IONONE; CARBOMER HOMOPOLYMER TYPE B (ALLYL SUCROSE CROSSLINKED); GERANIOL; DISODIUM STEAROYL GLUTAMATE; EDETATE DISODIUM; CETYL ALCOHOL; CETOSTEARYL ALCOHOL; METHYLPARABEN; CETEARYL GLUCOSIDE; BUTYLPHENYL METHYLPROPIONAL; .BETA.-CITRONELLOL, (R)-; BUTYLENE GLYCOL; COUMARIN

Drug Facts

Active ingredients

Avobenzone 3%
Octisalate 5%
Octocrylene 3%

Purpose

Sunscreen

Uses

- helps prevent sunburn

- if used as directed with other sun protection measures (see Directions), decreases the risk of skin cancer and early skin aging caused by the sun

Warnings

For external use only

Do not use

on damaged or broken skin

When using this product

keep out of eyes. Rinse with water to remove.

Stop use and ask a doctor if

rash occurs

Keep out of reach of children.

If swallowed, get medical help or contact a Poison Control Center right away.

Directions

For sunscreen use:

● apply generously and evenly 15 minutes before sun exposure

● reapply at least every 2 hours

● use a water resistant sunscreen if swimming or sweating

● Sun Protection Measures. Spending time in the sun increases your risk of skin cancer and early skin aging. To decrease this risk, regularly use a sunscreen with a Broad Spectrum SPF value of 15 or higher and other sun protection measures including:

● limit time in the sun, especially from 10 a.m. – 2 p.m.

● wear long-sleeved shirts, pants, hats, and sunglasses

● children under 6 months of age: Ask a doctor

Other information

protect the product in this container from excessive heat and direct sun

Inactive ingredients

water, glycerin, dimethicone, PTFE, octyldodecanol, alcohol denat., isopropyl isostearate, methylsilanol/silicate crosspolymer, arachidyl alcohol, tocopheryl acetate, medicago sativa (alfalfa) extract, hydrolyzed rice protein, sodium chloride, sodium hyaluronate, phenoxyethanol, acetyl trifluoromethylphenyl valylglycine, adenosine, PEG-100 stearate, behenyl alcohol, polysorbate 80, silica, cellulose acetate butyrate, polyphosphorylcholine glycol acrylate, polyvinyl alcohol, dimethicone/vinyl dimethicone crosspolymer, ammonium acryloyldimethyltaurate/steareth-25 methacrylate crosspolymer, dimethiconol, limonene, ammonium polyacryloyldimethyl taurate, manganese gluconate, linalool, benzyl alcohol, isohexadecane, capryloyl salicylic acid, alpha-isomethyl ionone, acrylamide/sodium acryloyldimethyltaurate copolymer, carbomer, geraniol, disodium stearoyl glutamate, disodium EDTA, cetyl alcohol, cetearyl alcohol, methylparaen, cetearyl glucoside, butylphenyl methylpropional, methylisothiazolinone, citronellol, butylene glycol, coumarin, fragrance

Questions or comments?

1-800-LANCOME (1-800-526-2663)

Monday - Friday (9 a.m. - 5 p.m. EST)